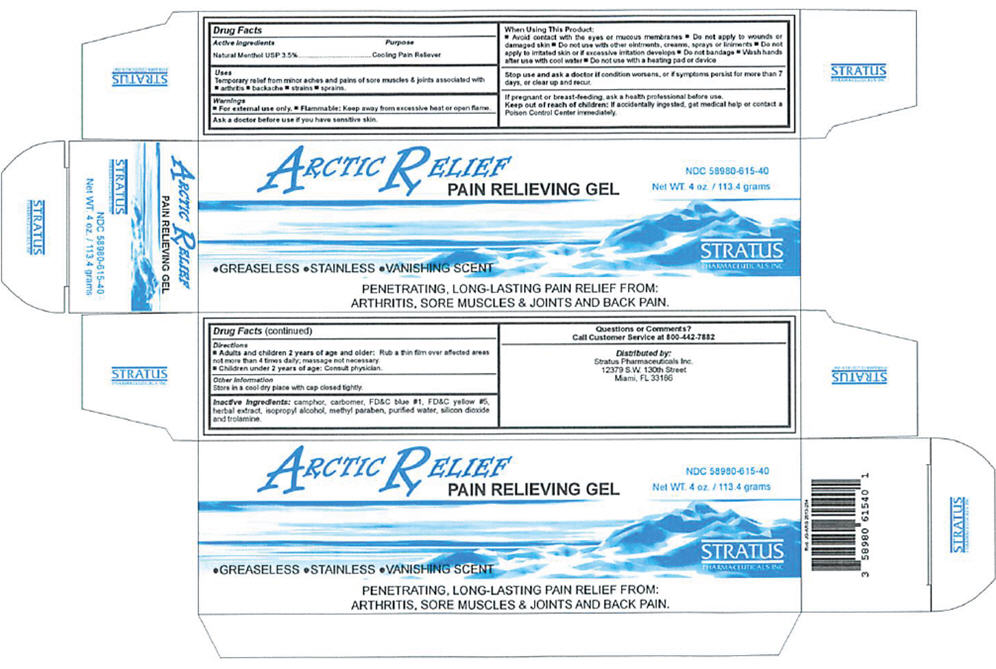 DRUG LABEL: ARCTIC RELIEF
NDC: 58980-615 | Form: GEL
Manufacturer: STRATUS PHARMACEUTICALS INC
Category: otc | Type: HUMAN OTC DRUG LABEL
Date: 20241031

ACTIVE INGREDIENTS: MENTHOL, UNSPECIFIED FORM 3.969 g/113.4 g
INACTIVE INGREDIENTS: CAMPHOR (SYNTHETIC); CARBOMER HOMOPOLYMER TYPE C (ALLYL PENTAERYTHRITOL CROSSLINKED); FD&C BLUE NO. 1; FD&C YELLOW NO. 5; ILEX PARAGUARIENSIS LEAF; ISOPROPYL ALCOHOL

ARCTIC RELIEF

DRUG FACTS

Active Ingredient

Natural Menthol USP 3.5%

Purpose

Cooling Pain Reliever

Inactive Ingredients

Camphor, carbomer, FD&C blue #1, FD&C yellow #5, herbal extract, isopropyl alcohol, methyl paraben, silicon dioxide, trolamine and purified water.

Uses

Temporary relief from minor aches and pains of sore muscles & joints associated with

- arthritis
- backache
- strains
- sprains.

Warnings

FOR EXTERNAL USE ONLY.

Flammable: Keep away from excessive heat or open flame.

Ask a doctor before use if you have sensitive skin.

When Using This Product

- Avoid contact with the eyes or mucous membranes
- Do not apply to wounds or damaged skin
- Do not use with other ointments, creams, sprays or liniments
- Do not apply to irritated skin or if excessive irritation develops
- Do not bandage
- Wash hands after use with cool water
- Do not use with a heating pad or device.

Stop Use And Ask A Doctor If

Condition worsens, or if symptoms persist for more than 7 days, or clear up and recur.

If pregnant or breast-feeding

Ask a health professional before use.

Keep out of reach of children: If accidentally ingested, get medical help or contact a Poison Control Center immediately.

Directions

- Adults and children 2 years of age and older: Rub a thin film over affected areas not more than 4 times daily; massage not necessary.
- Children under 2 years of age: Consult physician

Other Information

Store in a cool dry place with cap closed tightly

Questions or Comments?

Call Customer Service at 800-442-7882

Distributed by:
Stratus Pharmaceuticals Inc.
Miami, FL 33186

PRINCIPAL DISPLAY PANEL - 113.4 gram Tube Box

Arctic Relief
PAIN RELIEVING GEL

NDC 58980-615-40

Net WT. 4 oz. / 113.4 grams

•GREASELESS •STAINLESS •VANISHING SCENT

PENETRATING, LONG-LASTING PAIN RELIEF FROM:
ARTHRITIS, SORE MUSCLES & JOINTS AND BACK PAIN.

STRATUS
PHARMACEUTICALS INC